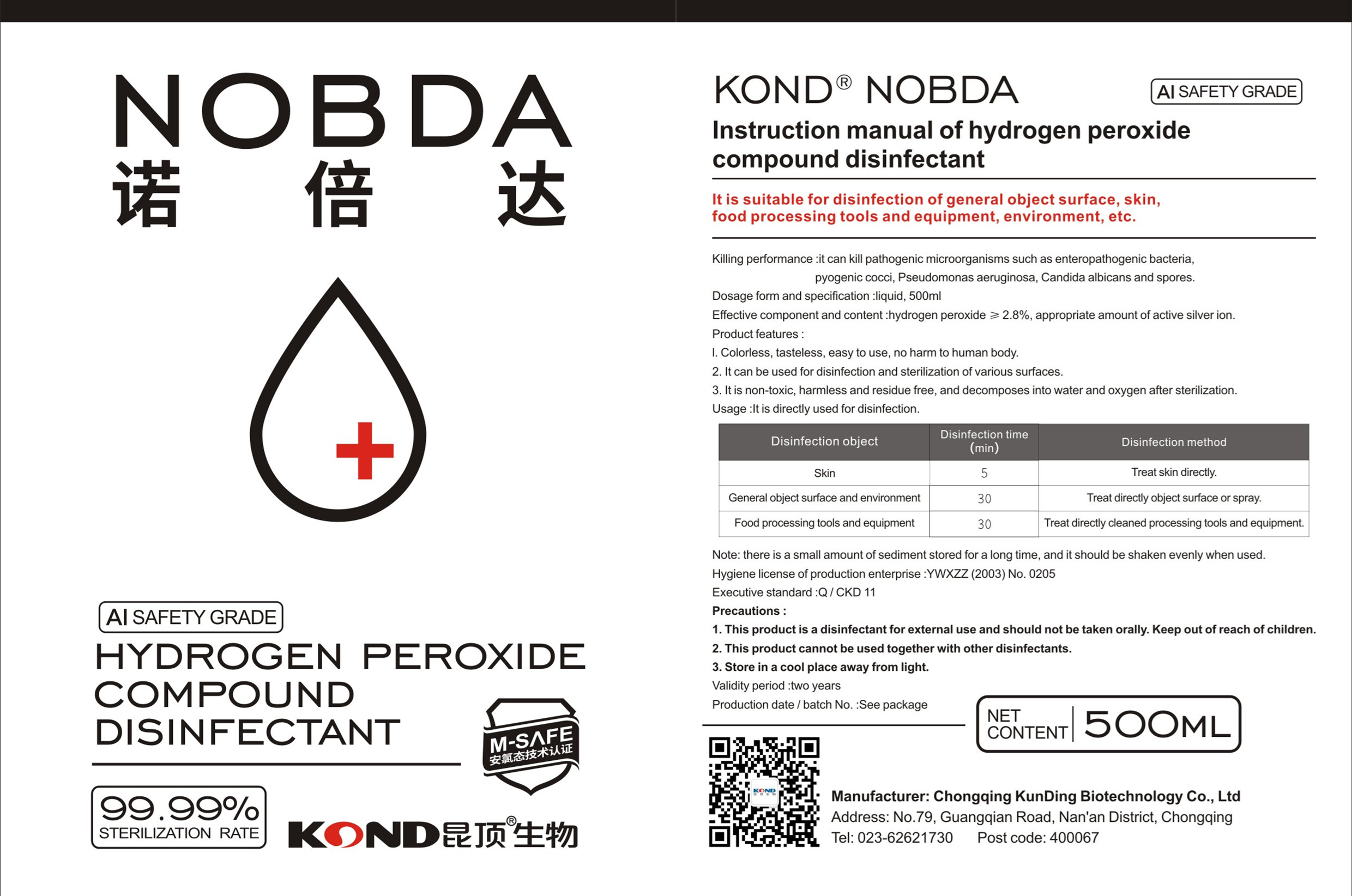 DRUG LABEL: Nobda Hydrogen peroxide compound disinfectant
NDC: 54520-003 | Form: LIQUID
Manufacturer: Chongqing Kunding Biologic Technology Co., Ltd.
Category: otc | Type: HUMAN OTC DRUG LABEL
Date: 20200409

ACTIVE INGREDIENTS: HYDROGEN PEROXIDE 15 mg/500 mL
INACTIVE INGREDIENTS: WATER

DOSAGE AND ADMINISTRATION

Tap the button two or three times

INACTIVE INGREDIENT

water

INDICATIONS AND USAGE

It can be used for disinfection and serilization of various surfaces

ACTIVE INGREDIENT

Hydrogen peroxide

keep out of children

PURPOSE

it can kill pathogenic microorganisms such as enteropathogenic bacteria,pyogenic cocci, Pseudomonas aeruginosa, Candida albicans and spores.

WARNINGS

1. This product is a disinfectant for external use and should not be taken orally. Keep out of reach of children.
2. This product cannot be used together with other disinfectants.
3. Store in a cool place away from light.